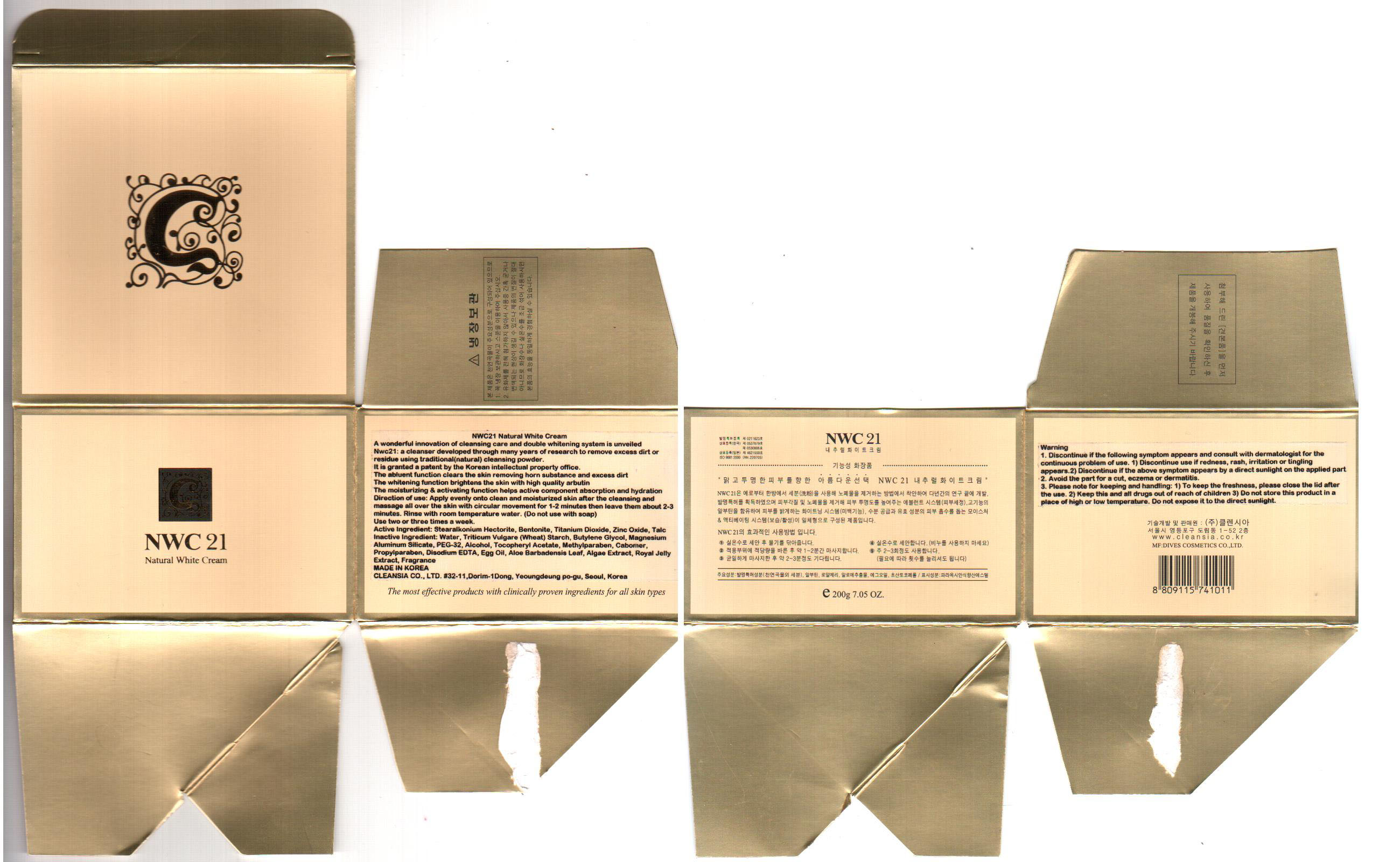 DRUG LABEL: NWC21 NATURAL WHITE CREAM
NDC: 45167-167 | Form: CREAM
Manufacturer: Cleansia Co Ltd
Category: otc | Type: HUMAN OTC DRUG LABEL
Date: 20100124

ACTIVE INGREDIENTS: TITANIUM DIOXIDE 2 g/200 g; ZINC OXIDE 0.8 g/200 g

Active Ingredients:
Stearalkorium Hectorite, Bentonite, Titanium Dioxide, Zinc Oxide, Talc

Inactive Ingredients:
Water, Triticum Vulgare (Wheat) Starch, Butylene Glycol, Magnesium Aluminum Silicate, PEG-32, Alcohol, Tocopheryl Acetate, Methylparaben, Cabomer, Propylparaben, Disodium EDTA, Egg Oil, Aloe Barbadensis Leaf, Algae Extract, Royal Jelly Extract, Fragrance

WHEN USING

Direction of use:
Apply evenly onto clean and moisturized skin after the cleansing and massage all over the skin with circular movement for 1-2 minutes. Then leave them about 2-3 minutes. Rinse with room temperature water (do not use with soap). Use two or three times a week.

KEEP OUT OF REACH OF CHILDREN

Keep this and all drugs out of reach of children

Warning:
1. Discontinue if the following symptom appears and consult with dermatologist for the continuous problem of use
a) Discontinue use if redness, rash, irritation or tingling appears
b) Discontinue if the above symptom appears by a direct sunlight on the applied part
2. Avoid the part for a cut, eczema or dermatitis

Storage and Handling:
- To keep the freshness, please close the lid after the use
- Do not store this product in a place of high or low temperature
- Do not expose it to the direct sunlight